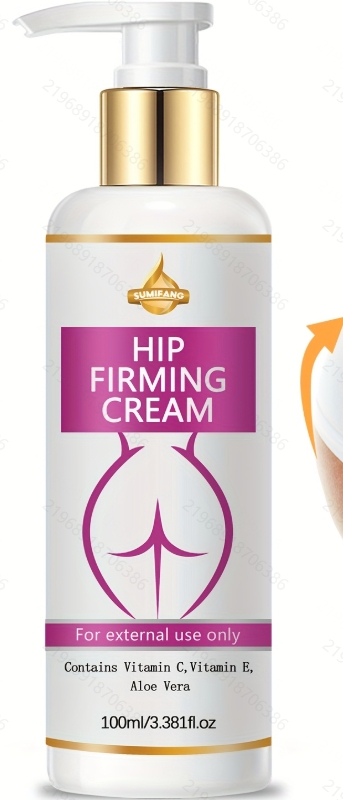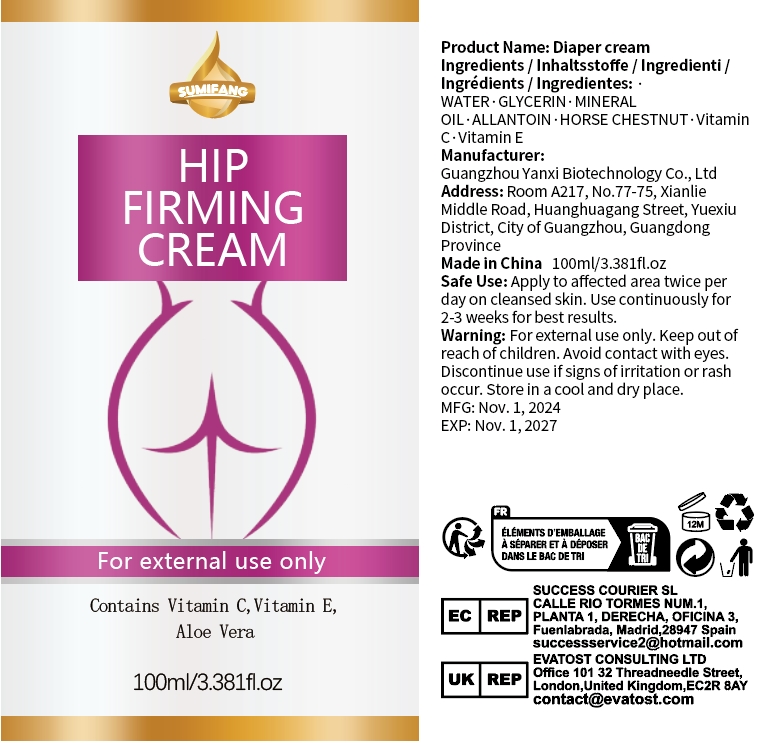 DRUG LABEL: Diaper cream
NDC: 84025-306 | Form: CREAM
Manufacturer: Guangzhou Yanxi Biotechnology Co., Ltd
Category: otc | Type: HUMAN OTC DRUG LABEL
Date: 20250106

ACTIVE INGREDIENTS: MINERAL OIL 3 mg/100 mL; GLYCERIN 5 mg/100 mL
INACTIVE INGREDIENTS: WATER

WARNINGS

Keep out of children

INACTIVE INGREDIENT

Aqua

DOSAGE AND ADMINISTRATION

Apply to affected area twice per dayon cleansed skin.Use continuously for 2-3 weeks for best results.

INDICATIONS AND USAGE

For daily skin care

Keep out of children

PURPOSE

Keep Hip firming and moisturizing